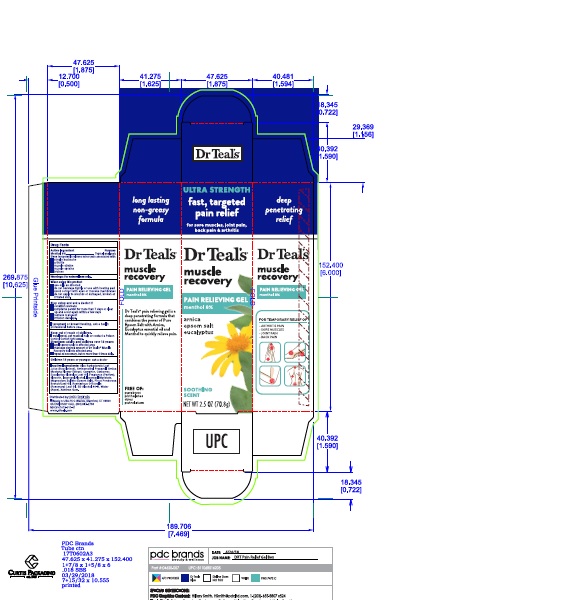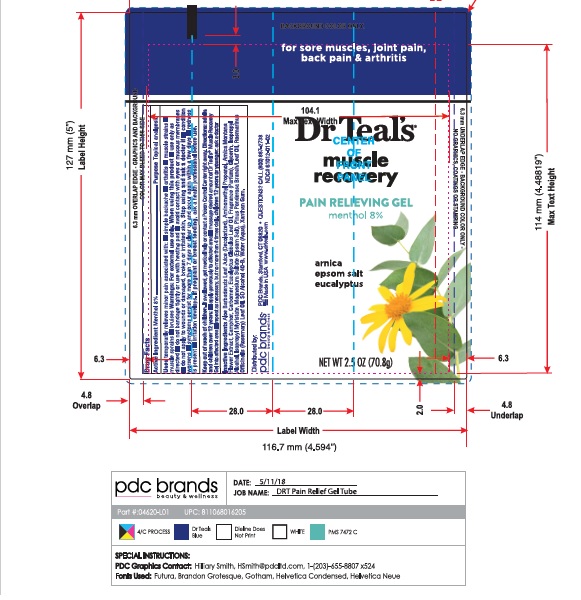 DRUG LABEL: Dr. Teals
NDC: 61012-011 | Form: GEL
Manufacturer: PDC Brands
Category: otc | Type: HUMAN OTC DRUG LABEL
Date: 20191226

ACTIVE INGREDIENTS: MENTHOL 80 mg/1 g
INACTIVE INGREDIENTS: GLYCERIN; XANTHAN GUM; EUCALYPTUS OIL; CARBOMER HOMOPOLYMER TYPE A (ALLYL PENTAERYTHRITOL CROSSLINKED); ISOPROPYL ALCOHOL; PINUS PINASTER SEED OIL; MAGNESIUM SULFATE HEPTAHYDRATE; WATER; ALOE VERA LEAF; ALCOHOL; CAMPHOR OIL, WHITE; ISOPROPYL MYRISTATE; ROSEMARY OIL; ARNICA MONTANA FLOWER; AMINOMETHYLPROPANOL

Dr. Teals Muscle Recovery Pain Gel 8%

Drug Facts

Active Ingredient | Purpose
Menthol 8% | Topical Analgesic

Stop using and ask a doctor if

- condition worsens
- symptoms persist for more than 7 days or clear up and occur again within a few days
- redness is pesent
- irritation develops

If pregnant or breast feeding, ask a health professional before use

DO NOT USE APPLY

do not apply to wouonds or damaged, broken or irritated skin

PREGNANCY OR BREAST FEEDING

If pregnant or breast feeding, ask a health professional before use

QUESTIONS

Distributed By:
pdc brands

PDC BRANDS, Stamford, CT 06820

Made in USA

www.drteals.com

Questions? CALL (800)887-2738
NDC#61012-011-02

Inactive Ingredients:

Aloe Barbadensis Leaf Juice (Decolorized), Aminomethylpropanol, Arnica Montana Flower Extract, Camphor, Carbomer, Eucalyptus Globulus Leaf oil, Fragrance (Parfum), Glycerin, Isopropyl Alcohol, Isopropyl Myristae, Magnesium Sulfate (Epsom salt), Pinus Ponderosa Branch/ Leaf Oil, Rosmarinus Officinalis (Rosemary) Leaf Oil, SD Alcohol 40-B, Water (Aqua), Xanthan Gum

Warnings

FOR EXTERNAL USE ONLY
when using this product
use only as directed
DO NOT BANDAGE TIGHTLY OR USE WITH HEATING PAD
avoid contact with eyes or mucous membranes
do not apply to wouonds or damaged, broken or irritated skin

USES

temporarily relieves minor pain associated with
Simple backache
arthritis
muscle strains
muscle sprains
bruises

DIRECTIONS

Adults and children over 12 years
apply generously to affected area
massage desired amount of Dr Teals Muscle Recovery Gel into affected area
repeat as necessary, but no more than 4 times daily
Children 12 years or younger:
ask a doctor

Keep out of reach of children. If swallowed, get medical help or contact a Poison Control Center right away

Uses:

- temporarily relieves minor pain associated with
- Simple backache
- arthritis
- muscle strains
- muscle sprains
- bruises

PACKAGE LABEL

Outer Box Art Work

Tube Art Work